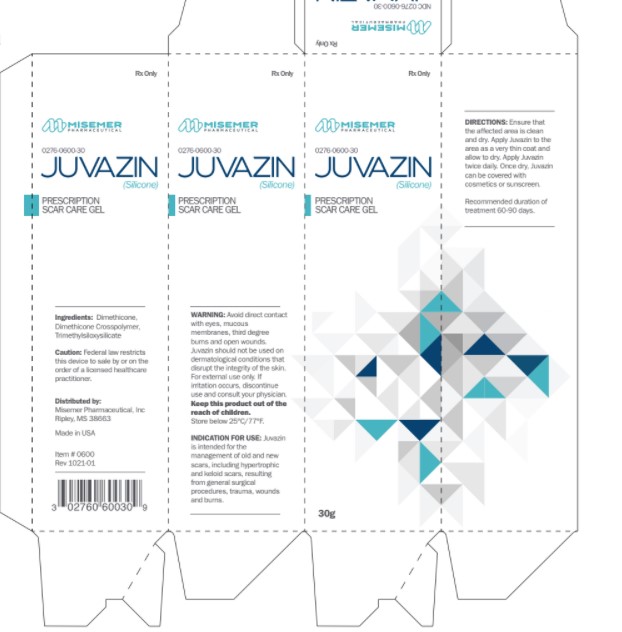 DRUG LABEL: Juvazin
NDC: 0276-0600
Manufacturer: Misemer Pharmaceutical
Category: other | Type: MEDICAL DEVICE
Date: 20190715
INACTIVE INGREDIENTS: TRIMETHYLSILOXYSILICATE (M/Q 0.6-0.8); DIMETHICONE CROSSPOLYMER (450000 MPA.S AT 12% IN CYCLOPENTASILOXANE); DIMETHICONE

Juvazin

INGREDIENTS

Dimethicone, Dimethicone Crosspolymer, Trimethylsiloxysilicate.

INDICATIONS AND USES

JuvazinTM is intended for the management of old and new scars, including hypertrophic and keloid scars, resulting from general surgical procedures, trauma, wounds and burns.

WARNINGS

Avoid direct contact with eyes, mucous membranes, third degree burns and open
wounds. JuvazinTM should not be used on dermatological conditions that disrupt the
integrity of the skin. For external use only. If irritation occurs, discontinue use and
consult your physician.
Keep this product out of the reach of children.
Store below 25°C/77°F.

PRECAUTIONS

Federal law restricts this device to sale by or on the order of a licensed healthcare
practitioner.
CALL YOUR DOCTOR ABOUT SIDE EFFECTS.
Call your doctor about side effects. You may report side effects to the FDA
at 1-800-FDA-1088.

DOSAGE AND ADMINISTRATION

Ensure that the affected area is clean and dry. Apply JuvazinTM to the area as a very
thin coat and allow to dry. Apply JuvazinTM twice daily. Once dry, JuvazinTM can be
covered with cosmetics or sunscreen. Recommended duration of treatment 60-90
days.